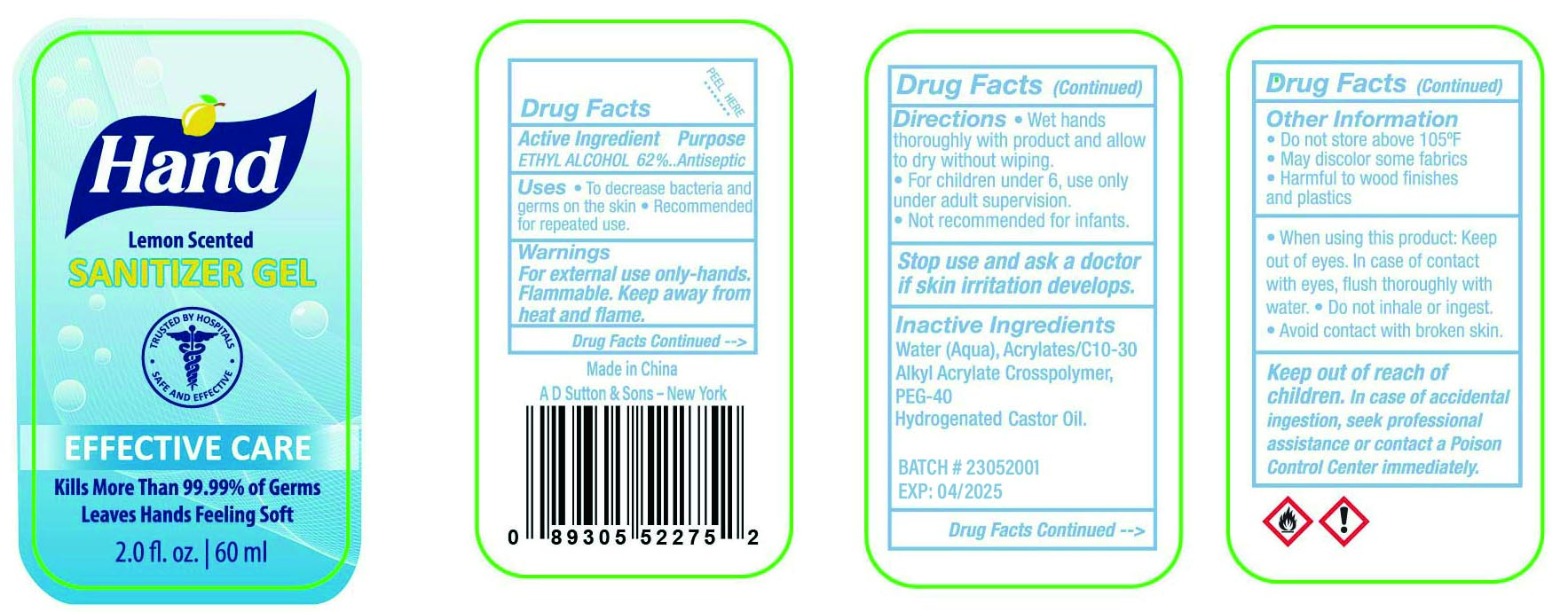 DRUG LABEL: hand sanitizer gel
NDC: 77975-025 | Form: GEL
Manufacturer: Guangzhou Tingcai Cosmetic Co., Ltd.
Category: otc | Type: HUMAN OTC DRUG LABEL
Date: 20230914

ACTIVE INGREDIENTS: ALCOHOL 62 mL/100 mL
INACTIVE INGREDIENTS: WATER; CARBOMER COPOLYMER TYPE A (ALLYL PENTAERYTHRITOL CROSSLINKED); POLYOXYL 40 HYDROGENATED CASTOR OIL

HAND SANITIZER

Active ingredient

ETHYL ALCOHOL 62%

Use

to decrease bacteria and germs on the skin ,recommended for repeated use

Warnings

for external use only-hands.flammable .keep away from heat and flame

Keep out of reach of children.

in case of accidental ingestion,seek professional assistance or contact a poison control center immediately.

Stop use and ask a doctor

if skin irritation develops.

Directions

Wet hands thoroughly with product and allow to dry without wiping.

For children under 6, use only under adult supervision.

Not recommended for infants.

Other Information

Do not store above 105 ℉

May discolor some fabrics

Harmful to wood finishes and plastics

When using this product:

Keep out of eyes.

In case of contact with eyes, flush thoroughly with water.

Do not inhale or ingest.
Avoid contact with broken skin.

Inactive ingredients

Water(Aqua),Acrylates/C10-30 Alkyl Acrylate Crosspolymer, PEG-40 Hydrogenated castor Oil